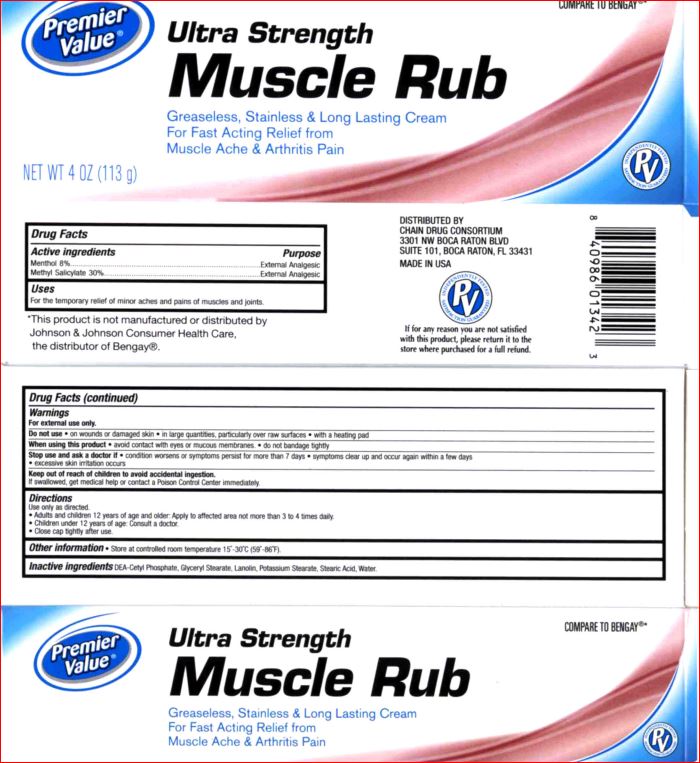 DRUG LABEL: Muscle Rub
NDC: 68016-186 | Form: CREAM
Manufacturer: Premier Value
Category: otc | Type: HUMAN OTC DRUG LABEL
Date: 20170926

ACTIVE INGREDIENTS: Menthol 8 g/106 mL; Methyl Salicylate 30 g/106 mL
INACTIVE INGREDIENTS: DIETHANOLAMINE CETYL PHOSPHATE; GLYCERYL MONOSTEARATE; Lanolin; Potassium Stearate; Stearic Acid; WATER

Drug Facts

Uses

For temporary relief if minor aches and pains of muscles and joints

Warnings

For external use only

Do not use • on wounds or damaged skin • in large quantities, particularity over raw surfaces • with a healing pad

When using this product avoid contact with eyes • do not bandage tightly or use with a heating pad

Stop use and ask a doctor if rash occurs
• condition worsens
• symptoms last more than 7 days or clear up and occur again within a few days
• irritation develops

Directions

Use only as directed
• adults and children 12 years of age and older: spray on affected area, not more than 3 to 4 times daily
• children under 12 years of age: consult a doctor

Inactive ingredients

DEA-Cetyl Phosphate
Glyceryl Stearate
Lanolin
Potassium Stearate
Stearic Acid
Water